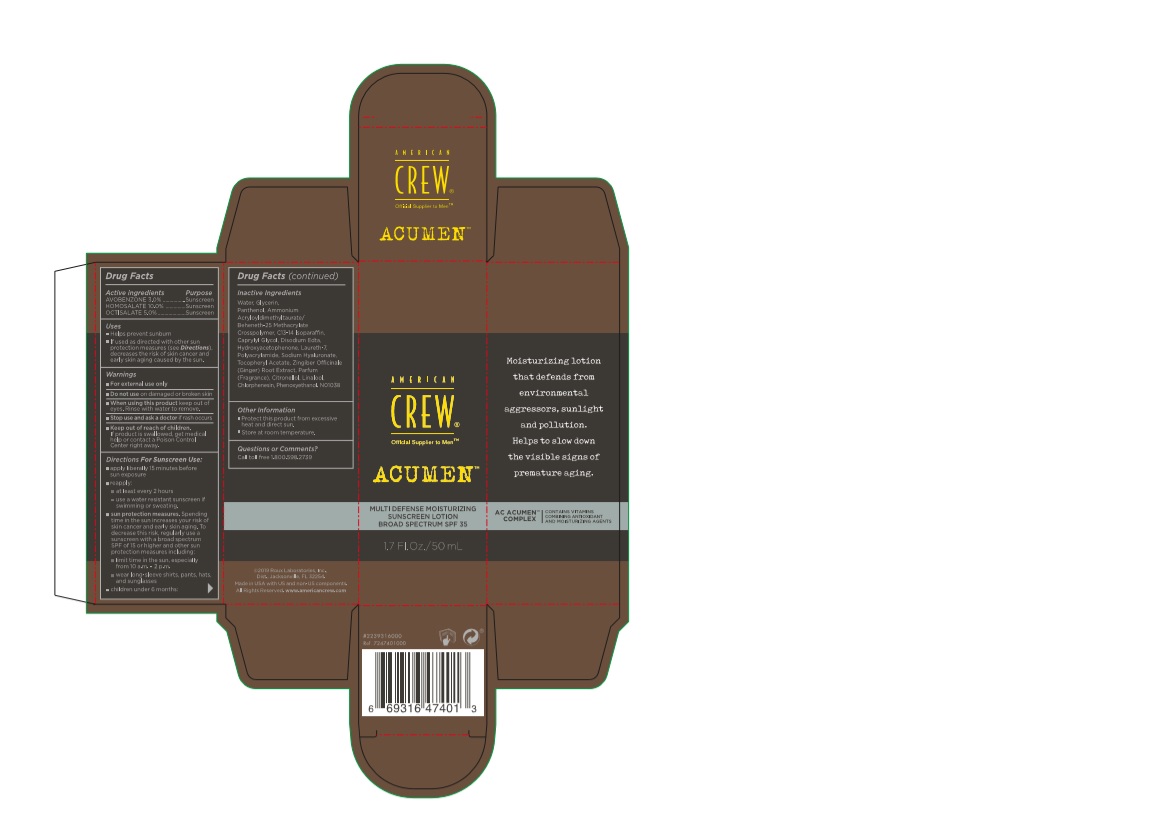 DRUG LABEL: American Crew Acumen Multi Defense Moisturizing Sunscreen
NDC: 10967-659 | Form: LOTION
Manufacturer: Revlon Consumer Products Corporation
Category: otc | Type: HUMAN OTC DRUG LABEL
Date: 20200114

ACTIVE INGREDIENTS: AVOBENZONE 3 mg/1 mL; HOMOSALATE 10 mg/1 mL; OCTISALATE 5 mg/1 mL
INACTIVE INGREDIENTS: EDETATE DISODIUM ANHYDROUS; HYDROXYACETOPHENONE; LAURETH-7; POLYACRYLAMIDE (10000 MW); GINGER; .ALPHA.-TOCOPHEROL ACETATE; .BETA.-CITRONELLOL, (R)-; HYALURONATE SODIUM; LINALOOL, (+)-; PHENOXYETHANOL; AMMONIUM ACRYLOYLDIMETHYLTAURATE/BEHENETH-25 METHACRYLATE CROSSPOLYMER (52000 MPA.S); CHLORPHENESIN; WATER; GLYCERIN; PANTHENOL; C13-14 ISOPARAFFIN; CAPRYLYL GLYCOL

Amercian Crew Acumen Multi Defense Moisturizing Sunscreen Lotion

Drug Facts

Avobenzone 3.0%

Homosalate 10.0%

Octisalate 5.0%

Purpose

Sunscreen

Uses

- Helps prevent sunburn

- If used as directed with other sun protection measures (see Directions), decreases the risk of skin cancer and early skin aging caused by the sun

Warnings

- For external use only

- Do not use on damaged or broken skin

- When using this product keep out of eyes. Rinse with water to remove.

- Stop use and ask a doctor is rash occurs.

- Keep out of reach of children. If product is swallowed get medical help or contact a Poison Control Center right away.

Directions For Sunscreen Use

- apply liberally 15 minutes before sun exposure

- repply:

- at least every 2 hours

- use a water resistant sunscreen if swimming or sweating

- sun protection measures. Spending time in the sun increases your risk of cancer and early skin aging. To decrease the risk, regularly use a sunscreen with a broad spectrum SPF or higher and other sun protection measures including:

- limit time in the sun, especially from 10 a.m. to 2p.m.

- wear long sleeve shirts, pants, hats and sunglasses

Storage

- Protect this product from excessive heat and direct sun

- Store at room temperature